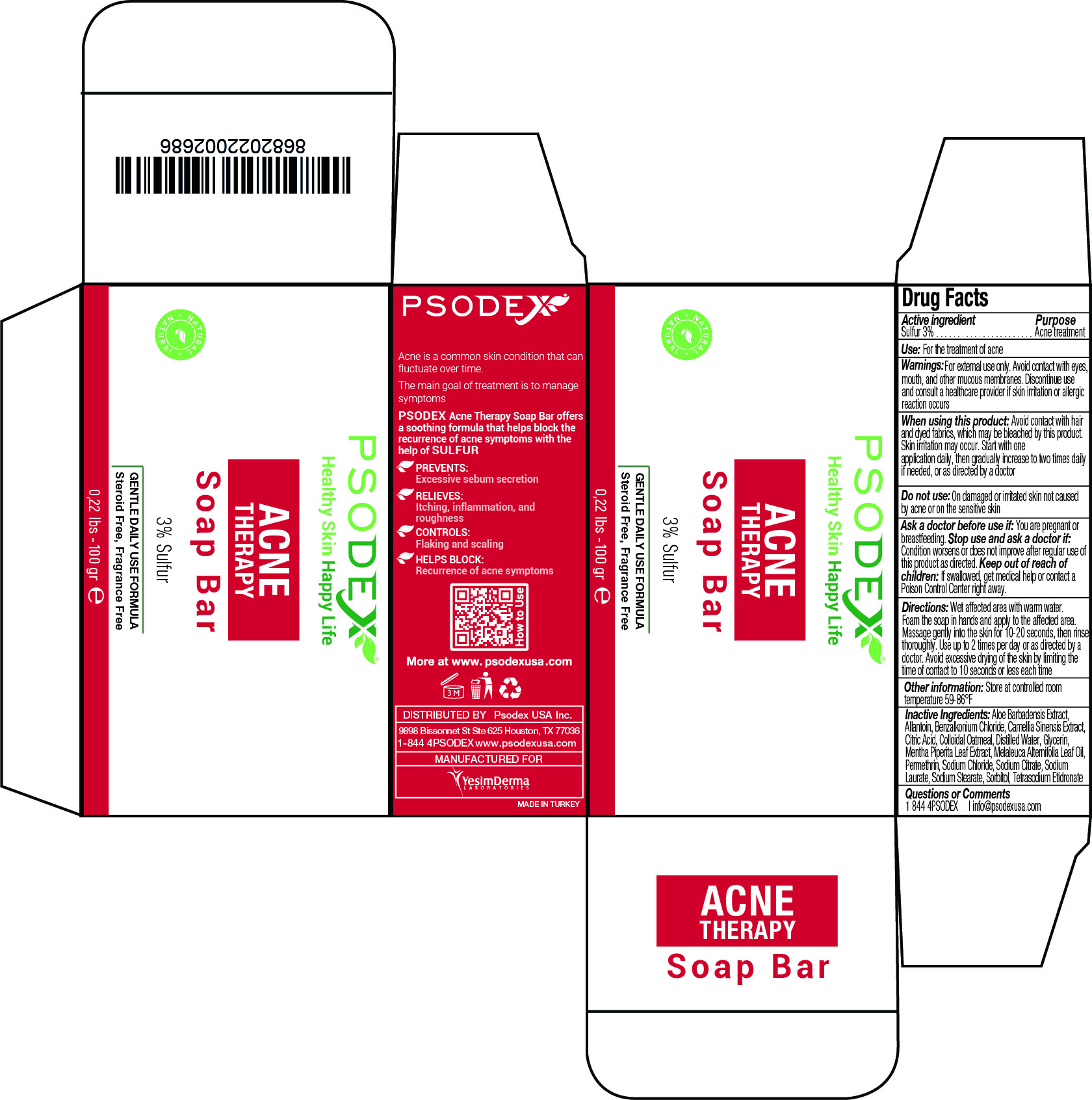 DRUG LABEL: Acne Therapy
NDC: 73503-013 | Form: SOAP
Manufacturer: PSODEX USA INC
Category: otc | Type: HUMAN OTC DRUG LABEL
Date: 20231221

ACTIVE INGREDIENTS: SULFUR 3 g/100 g
INACTIVE INGREDIENTS: SORBITOL 10 g/100 g; TEA LEAF OIL 5 g/100 g; PERMETHRIN 1 g/100 g; ETIDRONATE TETRASODIUM 0.25 g/100 g; ALLANTOIN 2 g/100 g; MELALEUCA ALTERNIFOLIA (TEA TREE) LEAF OIL 1 g/100 g; SODIUM CHLORIDE 0.25 g/100 g; BENZALKONIUM CHLORIDE 0.1 g/100 g; MENTHA PIPERITA LEAF 7 g/100 g; SODIUM LAURATE 10 g/100 g; ALOE VERA LEAF 7 g/100 g; OATMEAL 2 g/100 g; SODIUM CITRATE 0.25 g/100 g; CITRIC ACID MONOHYDRATE 0.25 g/100 g; WATER 17 mL/100 g; SODIUM STEARATE 10 g/100 g; GLYCERIN 23.9 g/100 g

Anti Acne Soap Bar

DESCRIPTION

Acne is a common skin condition that can fluctuate over time.

The main goal of treatment is to manage symptoms.

PSODEX Acne Therapy Soap Bar offers a soothing formula that helps block the recurrence of acne symptoms with the help of SULFUR.

PREVENTS:
Excessive sebum secretion

RELIEVES:
Itching, inflammation, and roughness

CONTROLS:
Flaking and scaling

HELPS BLOCK:
Recurrence of acne symptoms

Active Ingredient / Purpose

Active ingredient: Sulfur 3%

Purpose: Acne treatment

Active ingredient: Sulfur 3%
Purpose: Acne treatment

Purpose: Acne treatment

Inactive Ingredients

Aloe Barbadensis Extract,
Allantoin, Benzalkonium Chloride, Camellia Sinensis Extract,
Citric Acid, Colloidal Oatmeal, Distilled Water, Glycerin,
Mentha Piperita Leaf Extract, Melaleuca Alternifolia Leaf Oil,
Permethrin, Sodium Chloride, Sodium Citrate, Sodium
Laurate, Sodium Stearate, Sorbitol, Tetrasodium Etidronate

USE

Use: For the treatment of acne

INFORMATION FOR OWNERS/CAREGIVERS

DISTRIBUTED BY: Psodex USA Inc.

9898 Bissonnet St Ste 625 Houston, TX 77036

1-844 4PSODEX www.psodexusa.com

MANUFACTURED FOR

Yesim Derma Laboratories

Directions:

Wet affected area with warm water. Foam the soap in hands and apply to the affected area. Massage gently into the skin for 10-20 seconds, then rinse thoroughly. Use up to 2 times per day or as directed by a doctor. Avoid excessive drying of the skin by limiting the

time of contact to 10 seconds or less each time

Ask a doctor before use if:

You are pregnant or breastfeeding.

Ask a doctor before use if:

You are pregnant or breastfeeding.

Stop use and ask a doctor if:

Condition worsens or does not improve after regular use of this product as directed.

Questions or Comments:

1 844 4PSODEX | info@psodexusa.com

Keep out of reach of children:

If swallowed, get medical help or contact a Poison Control Center right away.

Do not use :

On damaged or irritated skin not caused by acne or on the sensitive skin

When using this product :

Avoid contact with hair and dyed fabrics, which may be bleached by this product.
Skin irritation may occur. Start with one application daily, then gradually increase to two times daily if needed, or as directed by a doctor

Other information :

Store at controlled room temperature 59-86°F

Warnings:

For external use only